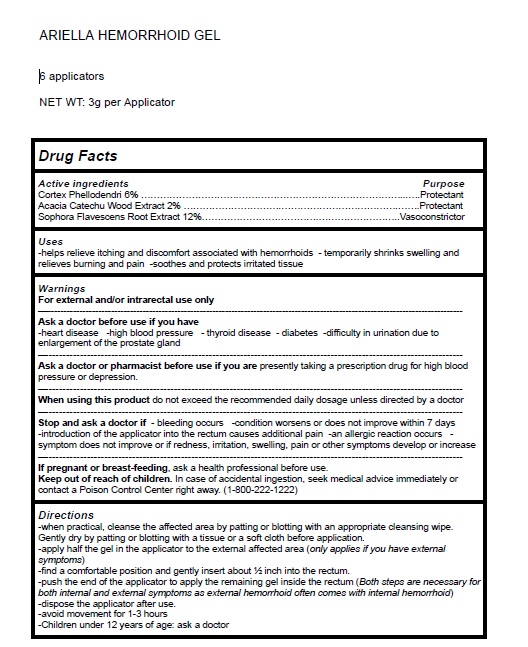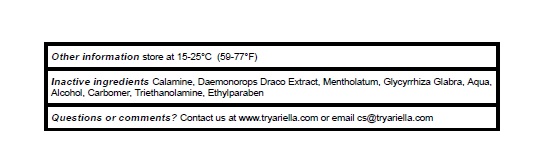 DRUG LABEL: Ariella Hemorrhoid Gel
NDC: 83364-002 | Form: GEL
Manufacturer: YITONGBADA (SHENZHEN) INTERNATIONAL TRADE CO., LTD
Category: otc | Type: HUMAN OTC DRUG LABEL
Date: 20230511

ACTIVE INGREDIENTS: PHELLODENDRON CHINENSE WHOLE 6 g/100 g; SENEGALIA CATECHU WOOD 2 g/100 g; SOPHORA FLAVESCENS ROOT 12 g/100 g
INACTIVE INGREDIENTS: ZINC OXIDE; CALAMUS DRACO WHOLE; MENTHOL, UNSPECIFIED FORM; GLYCYRRHIZA GLABRA; WATER; ALCOHOL; CARBOMER HOMOPOLYMER, UNSPECIFIED TYPE; TROLAMINE; ETHYLPARABEN

Active Ingredient Purpose

Cortex Phellodendri 6% Protectant

Acacia Catechu Wood Extract 2% Protectant

Sophora Flavescens Root Extract 12% Vasoconstrictor

Uses

helps relieve itching and discomfort associated with hemorrhoids - temporarily shrinks swelling and relieves burning and pain -soothes and protects irritated tissue

Warnings

For external use only.

Ask a doctorbefore use if you have heart disease -high blood pressure - thyroid disease - diabetes -difficulty in urination due to enlargement of the prostate gland

Ask a doctor or pharmacist before use if you are presently taking a prescription drug for high blood pressure or depression.

When using this product do not exceed the recommended daily dosage unless directed by a doctor

Stop and ask a doctor if - bleeding occurs -condition worsens or does not improve within 7 days introduction of the applicator into the rectum causes additional pain -an allergic reaction occurs - symptom does not improve or if redness, irritation, swelling, pain or other symptoms develop or increase

If pregnant or breast-feeding, ask a health professional before use.

Keep out of reach of children. In case of accidental ingestion, seek medical advice immediately or contact a Poison Control Center right away. (1-800-222-1222)

Directions

- when practical, cleanse the affected area by patting or blotting with an appropriate cleansing wipe.
- Gently dry by patting or blotting with a tissue or a soft cloth before application.
- apply half the gel in the applicator to the external affected area (only applies if you have external symptoms)
- find a comfortable position and gently insert about ½ inch into the rectum.
- push the end of the applicator to apply the remaining gel inside the rectum (Both steps are necessary for both internal and external symptoms as external hemorrhoid often comes with internal hemorrhoid)
- dispose the applicator after use.
- avoid movement for 1-3 hours
- Children under 12 years of age: ask a doctor

Other information

store at 15-25°C (59-77°F)

Inactive ingredients

Calamine, Daemonorops Draco Extract, Mentholatum, Glycyrrhiza Glabra, Aqua, Alcohol, Carbomer, Triethanolamine, Ethylparaben

Questions or comments?

Contact us at www.tryariella.com or email cs@tryariella.com